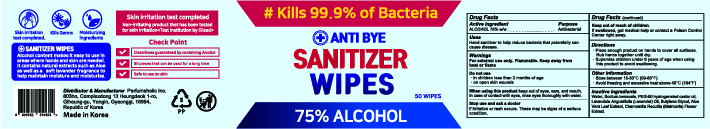 DRUG LABEL: ANTI BYE SANITIZER WIPES
NDC: 75773-375 | Form: CLOTH
Manufacturer: Perfumeholic Inc
Category: otc | Type: HUMAN OTC DRUG LABEL
Date: 20200928

ACTIVE INGREDIENTS: ALCOHOL 0.75 1/1 1
INACTIVE INGREDIENTS: BUTYLENE GLYCOL; WATER; ALOE VERA LEAF; CHAMOMILE; PEG-60 HYDROGENATED CASTOR OIL; LAVENDER OIL; SODIUM BENZOATE

Perfumeholic Inc | ANTI BYE SANITIZER WIPES | 75773-375-50 | 50 WIPES